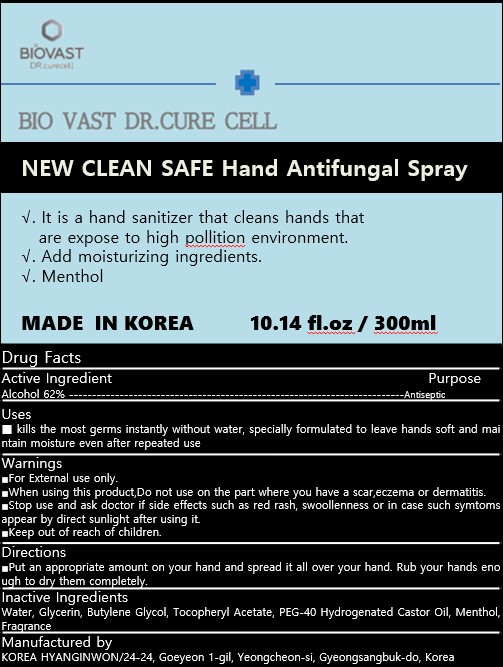 DRUG LABEL: BIO VAST DR.CURE CELL NEW CLEAN SAFE Hand Antifungal
NDC: 81259-200 | Form: SPRAY
Manufacturer: KOREA HYANGINWON
Category: otc | Type: HUMAN OTC DRUG LABEL
Date: 20210120

ACTIVE INGREDIENTS: ALCOHOL 186 mL/300 mL
INACTIVE INGREDIENTS: GLYCERIN 36 mL/300 mL; 1,3-BUTYLENE GLYCOL 1-PROPIONATE 6 mL/300 mL; WATER 60 mL/300 mL; .ALPHA.-TOCOPHEROL ACETATE, D- 6 mL/300 mL; MENTHOL 0.6 mL/300 mL; POLYOXYL 40 HYDROGENATED CASTOR OIL 24 mL/300 mL

Drug Facts

ACTIVE INGREDIENT

Alcohol 62%

PURPOSE

Antiseptic

Uses

kills the most germs instantly without water, specially formulated to leave hands soft and maintain moisture even after repeated use

Warnings

For External use only.

When using this product,Do not use on the part where you have a scar,eczema or dermatitis.

Stop use and ask doctor if side effects such as red rash, swoollenness or in case such symtoms appear by direct sunlight after using it.

Keep out of reach of children.

Keep out of reach of children.

Directions

Put an appropriate amount on your hand and spread it all over your hand. Rub your hands enough to dry them completely.

Inactive ingredients

Water, Glycerin, Butylene Glycol, Tocopheryl Acetate, PEG-40 Hydrogenated Castor Oil, Menthol, Fragrance